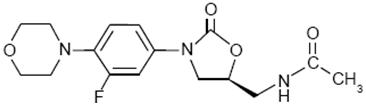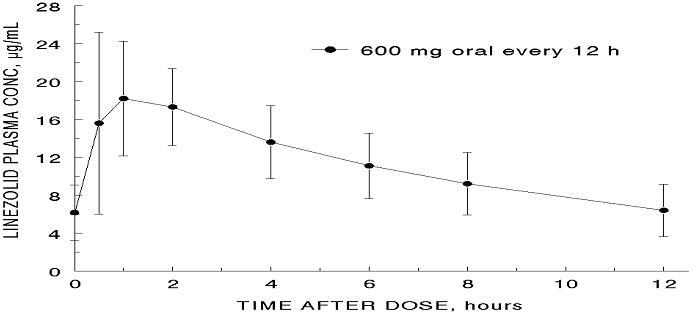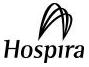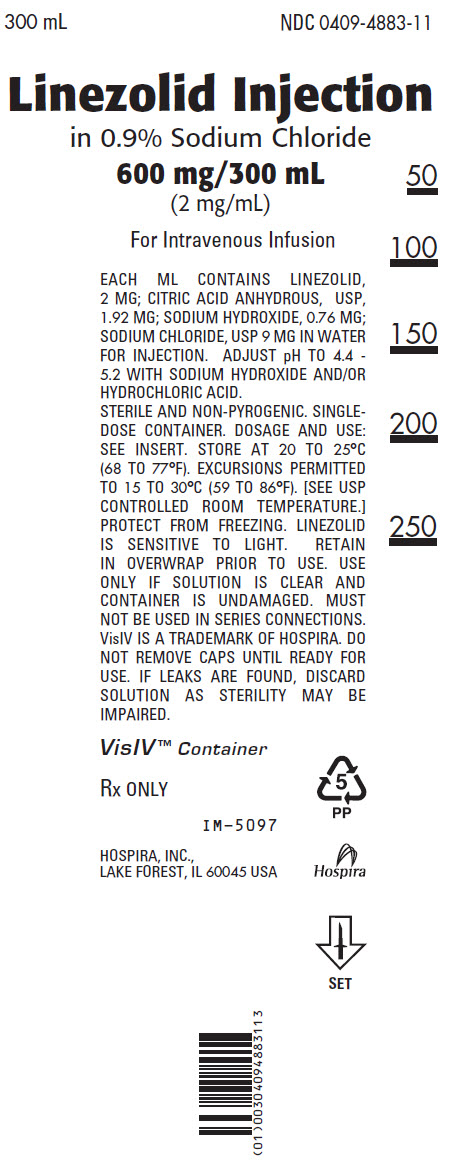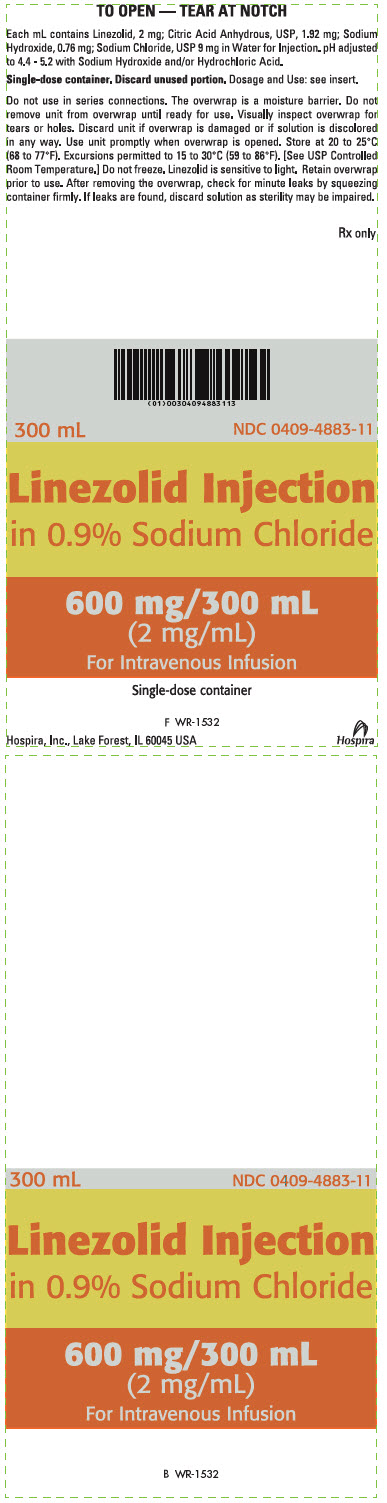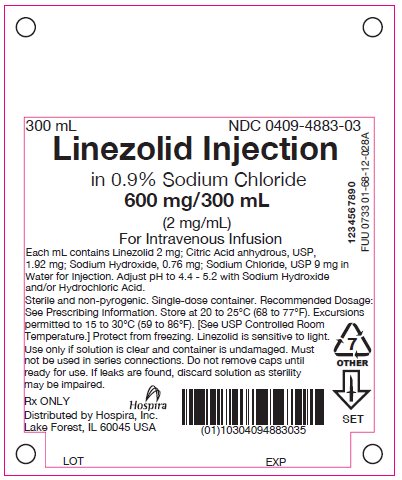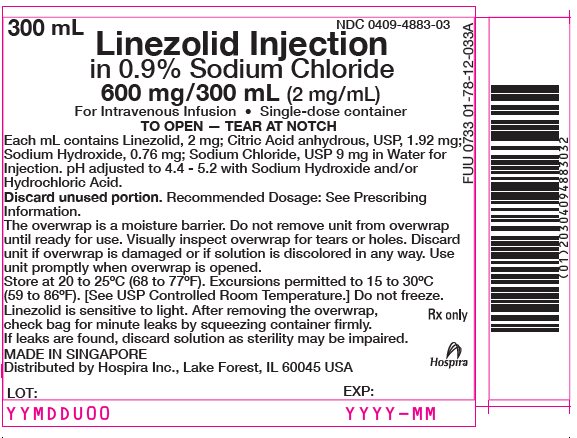 DRUG LABEL: Linezolid
NDC: 0409-4883 | Form: INJECTION, SOLUTION
Manufacturer: Hospira, Inc.
Category: prescription | Type: HUMAN PRESCRIPTION DRUG LABEL
Date: 20250606

ACTIVE INGREDIENTS: LINEZOLID 2 mg/1 mL
INACTIVE INGREDIENTS: SODIUM HYDROXIDE 0.76 mg/1 mL; ANHYDROUS CITRIC ACID 1.92 mg/1 mL; SODIUM CHLORIDE 9 mg/1 mL; WATER; HYDROCHLORIC ACID

HIGHLIGHTS OF PRESCRIBING INFORMATION

These highlights do not include all the information needed to use LINEZOLID injection safely and effectively. See full prescribing information for LINEZOLID injection.
LINEZOLID injection, for intravenous use
Initial U.S. Approval: 2000

RECENT MAJOR CHANGES

Warnings and Precautions, Rhabdomyolysis (5.9) | 5/2025

1 INDICATIONS AND USAGE

Linezolid injection is an oxazolidinone-class antibacterial indicated in adults and children for the treatment of the following infections caused by susceptible Gram-positive bacteria: Nosocomial pneumonia (1.1); Community-acquired pneumonia (1.2); Complicated skin and skin structure infections, including diabetic foot infections, without concomitant osteomyelitis (1.3); Vancomycin-resistant Enterococcus faecium infections. (1.4)
Limitations of Use: (1.5)

- Linezolid injection is not indicated for the treatment of Gram-negative infections.
- The safety and efficacy of Linezolid formulations given for longer than 28 days have not been evaluated in controlled clinical trials.

To reduce the development of drug-resistant bacteria and maintain the effectiveness of Linezolid injection formulations and other antibacterial drugs, Linezolid injection should be used only to treat or prevent infections that are proven or strongly suspected to be caused by bacteria. (1.6)

2 DOSAGE AND ADMINISTRATION

 | Dosage, Route, and Frequency of Administration
Infection | Pediatric Patients (Birth through 11 Years of Age) | Adults and Adolescents (12 Years and Older) | Duration (days)
Nosocomial pneumonia (1.1) | 10 mg/kg intravenously every 8 hours | 600 mg intravenously every 12 hours | 10 to 14
Community-acquired pneumonia, including concurrent bacteremia (1.2) | 10 mg/kg intravenously every 8 hours | 600 mg intravenously every 12 hours | 10 to 14
Complicated skin and skin structure infections (1.3) | 10 mg/kg intravenously every 8 hours | 600 mg intravenously every 12 hours | 10 to 14
Vancomycin-resistant Enterococcus faecium infections, including concurrent bacteremia (1.4) | 10 mg/kg intravenously every 8 hours | 600 mg intravenously every 12 hours | 14 to 28

- Pediatric Patients-The recommended dose is 10 mg per kg intravenously every 8 hours. Linezolid injection in a single-dose container should be used only in pediatric patients who require the entire 600 mg dose and not any fraction thereof. (2.1)

3 DOSAGE FORMS AND STRENGTHS

Injection: 600 mg/300 mL (2 mg/mL) linezolid. (3)

4 CONTRAINDICATIONS

- Known hypersensitivity to linezolid or any of the other product components. (4.1)
- Patients taking any monoamine oxidase inhibitors (MAOI) or within two weeks of taking an MAOI. (4.2)

5 WARNINGS AND PRECAUTIONS

- Myelosuppression: Monitor complete blood counts weekly. Thrombocytopenia has been reported more often in patients with severe renal and in patients with moderate to severe hepatic impairment. Consider discontinuation in patients who develop or have worsening myelosuppression. (5.1)
- Peripheral and Optic Neuropathy: Reported primarily in patients treated for longer than 28 days. If patients experience symptoms of visual impairment, prompt ophthalmic evaluation is recommended. (5.2)
- Serotonin Syndrome: Monitor patients taking serotonergic agents, including antidepressants and opioids, for signs of serotonin syndrome. Patients taking serotonergic antidepressants should receive Linezolid injection only if no other therapies are available. Discontinue serotonergic antidepressants and monitor patients for signs and symptoms of both serotonin syndrome and antidepressant discontinuation. (5.3)
- A mortality imbalance was seen in an investigational study in linezolid-treated patients with catheter-related bloodstream infections. (5.4)
- Clostridioides difficile-Associated Diarrhea: Evaluate if diarrhea occurs. (5.5)
- Potential interactions producing elevation of blood pressure: monitor blood pressure. (5.6)
- Rhabdomyolysis: If signs or symptoms of rhabdomyolysis are observed, discontinue Linezolid injection and initiate appropriate therapy. (5.9)
- Hypoglycemia: Postmarketing cases of symptomatic hypoglycemia have been reported in patients with diabetes mellitus receiving insulin or oral hypoglycemic agents. (5.10)
- Hyponatremia and/or Syndrome of Inappropriate Antidiuretic Hormone Secretion (SIADH): Monitor serum sodium levels regularly in patients at risk of hyponatremia and/or SIADH. (5.11)

6 ADVERSE REACTIONS

Most common adverse reactions (>5% of adult and pediatric patients treated with Linezolid injection) include: diarrhea, vomiting, headache, nausea, and anemia. (6)
To report SUSPECTED ADVERSE REACTIONS, contact Pfizer Inc. at 1-800-438-1985, or FDA at 1-800-FDA-1088 or www.fda.gov/medwatch.

7 DRUG INTERACTIONS

Monoamine oxidase inhibitors and potential for interaction with adrenergic and serotonergic agents. (4.2, 5.3, 5.6, 7, 12.3)

FULL PRESCRIBING INFORMATION

1 INDICATIONS AND USAGE

1.1 Nosocomial Pneumonia

Linezolid injection is indicated for the treatment of nosocomial pneumonia caused by Staphylococcus aureus (methicillin-susceptible and -resistant isolates) or Streptococcus pneumoniae [see Clinical Studies (14)].

1.2 Community-acquired Pneumonia

Linezolid injection is indicated for the treatment of community-acquired pneumonia caused by Streptococcus pneumoniae, including cases with concurrent bacteremia, or Staphylococcus aureus (methicillin-susceptible isolates only) [see Clinical Studies (14)].

1.3 Complicated Skin and Skin Structure Infections

Linezolid injection is indicated for the treatment of complicated skin and skin structure infections, including diabetic foot infections, without concomitant osteomyelitis, caused by Staphylococcus aureus (methicillin-susceptible and -resistant isolates), Streptococcus pyogenes, or Streptococcus agalactiae. Linezolid injection has not been studied in the treatment of decubitus ulcers [see Clinical Studies (14)].

1.4 Vancomycin-resistant Enterococcus faecium Infections

Linezolid injection is indicated for the treatment of vancomycin-resistant Enterococcus faecium infections, including cases with concurrent bacteremia [see Clinical Studies (14)].

1.5 Limitations of Use

- Linezolid injection is not indicated for the treatment of Gram-negative infections. It is critical that specific Gram-negative therapy be initiated immediately if a concomitant Gram-negative pathogen is documented or suspected [see Warnings and Precautions (5.4)].
- The safety and efficacy of Linezolid formulations given for longer than 28 days have not been evaluated in controlled clinical trials [see Clinical Studies (14)].

1.6 Usage

To reduce the development of drug-resistant bacteria and maintain the effectiveness of Linezolid injection and other antibacterial drugs, Linezolid injection should be used only to treat or prevent infections that are proven or strongly suspected to be caused by susceptible bacteria. When culture and susceptibility information are available, they should be considered in selecting or modifying antibacterial therapy. In the absence of such data, local epidemiology and susceptibility patterns may contribute to the empiric selection of therapy.

2 DOSAGE AND ADMINISTRATION

2.1 General Dosage and Administration

The recommended dosage for Linezolid injection for the treatment of infections is described in Table 1. No dose adjustment is necessary when switching from intravenous to oral administration.

Table 1. Dosage Guidelines for Linezolid Injection
 | Dosage, Route, and Frequency of Administration |  | Recommended Duration of Treatment (consecutive days)
Infection [Due to the designated pathogens [see Indications and Usage (1)]] | Pediatric Patients [Neonates less than 7 days: Most pre-term neonates less than 7 days of age (gestational age less than 34 weeks) have lower systemic linezolid clearance values and larger AUC values than many full-term neonates and older infants. These neonates should be initiated with a dosing regimen of 10 mg/kg every 12 hours. Consideration may be given to the use of 10 mg/kg every 8 hours regimen in neonates with a sub-optimal clinical response. All neonatal patients should receive 10 mg/kg every 8 hours by 7 days of life [see Use in Specific Populations (8.4) and Clinical Pharmacology (12.3)].] (Birth through 11 Years of Age) | Adults and Adolescents (12 Years and Older) | Recommended Duration of Treatment (consecutive days)
Nosocomial pneumonia | 10 mg/kg intravenously every 8 hours | 600 mg intravenously every 12 hours | 10 to 14
Community-acquired pneumonia, including concurrent bacteremia | 10 mg/kg intravenously every 8 hours | 600 mg intravenously every 12 hours | 10 to 14
Complicated skin and skin structure infections | 10 mg/kg intravenously every 8 hours | 600 mg intravenously every 12 hours | 10 to 14
Vancomycin-resistant Enterococcus faecium infections, including concurrent bacteremia | 10 mg/kg intravenously every 8 hours | 600 mg intravenously every 12 hours | 14 to 28

The maximum dose for pediatric patients should not exceed the recommended adult dose. The recommended dose is 10 mg per kg intravenously every 8 hours. Linezolid injection in a single-dose container should be used only in pediatric patients who require the entire 600 mg dose and not any fraction thereof.

2.2 Intravenous Administration

Linezolid injection is supplied in single-dose, ready-to-use container [see How Supplied/Storage and Handling (16)]. Parenteral drug products should be inspected visually for particulate matter prior to administration. Check for minute leaks by firmly squeezing the bag. If leaks are detected, discard the solution, as sterility may be impaired. Keep the containers in the overwrap until ready to use. Store at room temperature. Protect from freezing. Linezolid injection may exhibit a yellow color that can intensify over time without adversely affecting potency.

Linezolid injection should be administered by intravenous infusion over a period of 30 to 120 minutes. Do not use this intravenous container in series connections. Additives should not be introduced into this solution. If Linezolid injection is to be given concomitantly with another drug, each drug should be given separately in accordance with the recommended dosage and route of administration for each product. Discard unused portion.

If the same intravenous line is used for sequential infusion of several drugs, the line should be flushed before and after infusion of Linezolid injection with an infusion solution compatible with Linezolid injection and with any other drug(s) administered via this common line.

2.3 Compatibilities

Compatible intravenous solutions include 0.9% Sodium Chloride Injection, USP, 5% Dextrose Injection, USP, and Lactated Ringer's Injection, USP.

2.4 Incompatibilities

Physical incompatibilities resulted when Linezolid injection was combined with the following drugs during simulated Y-site administration: amphotericin B, chlorpromazine HCl, diazepam, pentamidine isothionate, erythromycin lactobionate, phenytoin sodium, and trimethoprim-sulfamethoxazole. Additionally, chemical incompatibility resulted when Linezolid injection was combined with ceftriaxone sodium.

3 DOSAGE FORMS AND STRENGTHS

Linezolid injection: 600 mg/300 mL (2 mg/mL) linezolid in single-dose, ready-to-use flexible plastic container in a foil laminate overwrap.

4 CONTRAINDICATIONS

4.1 Hypersensitivity

Linezolid injection is contraindicated for use in patients who have known hypersensitivity to linezolid or any of the other product components.

4.2 Monoamine Oxidase Inhibitors

Linezolid should not be used in patients taking any medicinal product which inhibits monoamine oxidases A or B (e.g., phenelzine, isocarboxazid) or within two weeks of taking any such medicinal product.

5 WARNINGS AND PRECAUTIONS

5.1 Myelosuppression

Myelosuppression (including anemia, leukopenia, pancytopenia, and thrombocytopenia) has been reported in patients receiving linezolid. In cases where the outcome is known, when linezolid was discontinued, the affected hematologic parameters have risen toward pretreatment levels. Thrombocytopenia has been reported more often in patients with severe renal impairment, whether or not on dialysis, and in patients with moderate to severe hepatic impairment. Complete blood counts should be monitored weekly in patients who receive linezolid, particularly in those who receive linezolid for longer than two weeks, those with pre-existing myelosuppression, those with severe renal impairment or moderate to severe hepatic impairment, those receiving concomitant drugs that produce bone marrow suppression, or those with a chronic infection who have received previous or concomitant antibacterial drug therapy. Discontinuation of therapy with linezolid should be considered in patients who develop or have worsening myelosuppression [see Adverse Reactions (6.2)].

5.2 Peripheral and Optic Neuropathy

Peripheral and optic neuropathies have been reported in patients treated with linezolid, primarily in those patients treated for longer than the maximum recommended duration of 28 days. In cases of optic neuropathy that progressed to loss of vision, patients were treated for extended periods beyond the maximum recommended duration. Visual blurring has been reported in some patients treated with linezolid for less than 28 days. Peripheral and optic neuropathy has also been reported in children.

If patients experience symptoms of visual impairment, such as changes in visual acuity, changes in color vision, blurred vision, or visual field defect, prompt ophthalmic evaluation is recommended. Visual function should be monitored in all patients taking Linezolid injection for extended periods (≥3 months) and in all patients reporting new visual symptoms regardless of length of therapy with Linezolid injection. If peripheral or optic neuropathy occurs, the continued use of Linezolid injection in these patients should be weighed against the potential risks.

5.3 Serotonin Syndrome

Spontaneous reports of serotonin syndrome including fatal cases associated with the co-administration of linezolid and serotonergic agents, including antidepressants such as selective serotonin reuptake inhibitors (SSRIs), have been reported.

Unless clinically appropriate and patients are carefully observed for signs and/or symptoms of serotonin syndrome or neuroleptic malignant syndrome-like (NMS-like) reactions, linezolid should not be administered to patients with carcinoid syndrome and/or patients taking any of the following medications: serotonin re-uptake inhibitors, tricyclic antidepressants, bupropion, buspirone, serotonin 5-HT1 receptor agonists (triptans), and opioids, including meperidine [see Drug Interactions (7) and Clinical Pharmacology (12.3)].

In some cases, a patient already receiving a serotonergic antidepressant or buspirone may require urgent treatment with linezolid. If alternatives to linezolid are not available and the potential benefits of linezolid outweigh the risks of serotonin syndrome or NMS-like reactions, the serotonergic antidepressant should be stopped promptly and linezolid administered. The patient should be monitored for two weeks (five weeks if fluoxetine was taken) or until 24 hours after the last dose of linezolid, whichever comes first. Symptoms of serotonin syndrome or NMS-like reactions include hyperthermia, rigidity, myoclonus, autonomic instability, and mental status changes that include extreme agitation progressing to delirium and coma. The patient should also be monitored for discontinuation symptoms of the antidepressant (see package insert of the specified agent(s) for a description of the associated discontinuation symptoms).

5.4 Mortality Imbalance in an Investigational Study in Patients With Catheter-Related Bloodstream Infections, Including Those With Catheter-Site Infections

An imbalance in mortality was seen in patients treated with linezolid relative to vancomycin/dicloxacillin/oxacillin in an open-label study in seriously ill patients with intravascular catheter-related infections [78/363 (21.5%) vs. 58/363 (16.0%); odds ratio 1.426, 95% CI 0.970, 2.098]. While causality has not been established, this observed imbalance occurred primarily in linezolid-treated patients in whom either Gram-negative pathogens, mixed Gram-negative and Gram-positive pathogens, or no pathogen were identified at baseline, but was not seen in patients with Gram-positive infections only.

Linezolid is not approved and should not be used for the treatment of patients with catheter-related bloodstream infections or catheter-site infections.

Linezolid has no clinical activity against Gram-negative pathogens and is not indicated for the treatment of Gram-negative infections. It is critical that specific Gram-negative therapy be initiated immediately if a concomitant Gram-negative pathogen is documented or suspected [see Indications and Usage (1)].

5.5 Clostridioides difficile-Associated Diarrhea

Clostridioides difficile-Associated Diarrhea (CDAD) has been reported with use of nearly all antibacterial agents, including linezolid, and may range in severity from mild diarrhea to fatal colitis. Treatment with antibacterial agents alters the normal flora of the colon leading to overgrowth of C. difficile.

C. difficile produces toxins A and B which contribute to the development of CDAD. Hypertoxin producing strains of C. difficile cause increased morbidity and mortality, as these infections can be refractory to antimicrobial therapy and may require colectomy. CDAD must be considered in all patients who present with diarrhea following antibacterial drug use.

Careful medical history is necessary since CDAD has been reported to occur over two months after the administration of antibacterial agents.

If CDAD is suspected or confirmed, ongoing antibacterial drug use not directed against C. difficile may need to be discontinued. Appropriate fluid and electrolyte management, protein supplementation, antibacterial drug treatment of C. difficile, and surgical evaluation should be instituted as clinically indicated.

5.6 Potential Interactions Producing Elevation of Blood Pressure

Unless patients are monitored for potential increases in blood pressure, linezolid should not be administered to patients with uncontrolled hypertension, pheochromocytoma, thyrotoxicosis and/or patients taking any of the following types of medications: directly and indirectly acting sympathomimetic agents (e.g., pseudoephedrine), vasopressive agents (e.g., epinephrine, norepinephrine), dopaminergic agents (e.g., dopamine, dobutamine) [see Drug Interactions (7) and Clinical Pharmacology (12.3)].

5.7 Lactic Acidosis

Lactic acidosis has been reported with the use of linezolid. In reported cases, patients experienced repeated episodes of nausea and vomiting. Patients who develop recurrent nausea or vomiting, unexplained acidosis, or a low bicarbonate level while receiving Linezolid injection should receive immediate medical evaluation.

5.8 Convulsions

Convulsions have been reported in patients when treated with linezolid. In some of these cases, a history of seizures or risk factors for seizures was reported.

5.9 Rhabdomyolysis

Rhabdomyolysis has been reported with the use of linezolid, including Linezolid injection [see Adverse Reactions (6.2)]. If signs or symptoms of rhabdomyolysis such as muscle pain, tenderness or weakness, dark urine or elevated creatine phosphokinase are observed, discontinue Linezolid injection and initiate appropriate therapy.

5.10 Hypoglycemia

Postmarketing cases of symptomatic hypoglycemia have been reported in patients with diabetes mellitus receiving insulin or oral hypoglycemic agents when treated with linezolid, a reversible, nonselective MAO inhibitor. Some MAO inhibitors have been associated with hypoglycemic episodes in diabetic patients receiving insulin or hypoglycemic agents. While a causal relationship between linezolid and hypoglycemia has not been established, diabetic patients should be cautioned of potential hypoglycemic reactions when treated with linezolid.

If hypoglycemia occurs, a decrease in the dose of insulin or oral hypoglycemic agent, or discontinuation of oral hypoglycemic agent, insulin, or linezolid may be required.

5.11 Hyponatremia and/or Syndrome of Inappropriate Antidiuretic Hormone Secretion (SIADH)

Postmarketing cases of hyponatremia and/or Syndrome of Inappropriate Antidiuretic Hormone Secretion (SIADH) have been observed in patients treated with linezolid. In reported cases, the signs and symptoms included confusion, somnolence, generalized weakness, and in severe cases led to respiratory failure and even death. Monitor serum sodium levels regularly in the elderly, in patients taking diuretics, and in other patients at risk of hyponatremia and/or SIADH while taking Linezolid injection. If signs and symptoms of hyponatremia and/or SIADH occur, discontinue Linezolid injection, and institute appropriate supportive measures.

5.12 Development of Drug-Resistant Bacteria

Prescribing Linezolid injection in the absence of a proven or strongly suspected bacterial infection or a prophylactic indication is unlikely to provide benefit to the patient and increases the risk of the development of drug-resistant bacteria.

6 ADVERSE REACTIONS

The following clinically significant adverse reactions are described elsewhere in the labeling:

- Myelosuppression [see Warnings and Precautions (5.1)]
- Peripheral and Optic Neuropathy [see Warnings and Precautions (5.2)]
- Serotonin Syndrome [see Warnings and Precautions (5.3)]
- Clostridioides difficile-Associated Diarrhea [see Warnings and Precautions (5.5)]
- Lactic Acidosis [see Warnings and Precautions (5.7)]
- Convulsions [see Warnings and Precautions (5.8)]
- Rhabdomyolysis [see Warnings and Precautions (5.9)]
- Hypoglycemia [see Warnings and Precautions (5.10)]
- Hyponatremia and/or Syndrome of Inappropriate Antidiuretic Hormone Secretion (SIADH) [see Warnings and Precautions (5.11)]

6.1 Clinical Trials Experience

Because clinical trials are conducted under widely varying conditions, adverse reaction rates observed in the clinical trials of a drug cannot be directly compared to rates in the clinical trials of another drug and may not reflect the rates observed in practice.

Adults

The safety of linezolid formulations was evaluated in 2,046 adult patients enrolled in seven Phase 3 comparator-controlled clinical trials, who were treated for up to 28 days. For all indications, 20.4% of linezolid-treated and 14.3% of comparator-treated patients experienced at least one drug-related adverse event.

Table 2 shows the incidence of all-causality, treatment-emergent adverse reactions reported in at least 1% of adult patients in these trials by dose of linezolid.

Table 2. Incidence (%) Treatment-Emergent Adverse Reactions Occurring in greater than 1% of Adult Patients Treated with Linezolid in Comparator-Controlled Clinical Trials
ADVERSE REACTIONS | Linezolid 600 mg every 12 hours (n = 1498) | All Other Comparators [Comparators included cefpodoxime proxetil 200 mg by mouth every 12 hours; ceftriaxone 1 g intravenously every 12 hours; dicloxacillin 500 mg by mouth every 6 hours; oxacillin 2 g intravenously every 6 hours; vancomycin 1 g intravenously every 12 hours.] (n = 1464)
Headache | 5.7 | 4.4
Diarrhea | 8.3 | 6.4
Nausea | 6.6 | 4.6
Vomiting | 4.3 | 2.3
Dizziness | 1.8 | 1.5
Rash | 2.3 | 2.6
Anemia | 2.1 | 1.4
Taste alteration | 1.0 | 0.3
Vaginal moniliasis | 1.1 | 0.5
Oral moniliasis | 1.7 | 1.0
Abnormal liver function tests | 1.6 | 0.8
Fungal infection | 0.3 | 0.2
Tongue discoloration | 0.3 | 0
Localized abdominal pain | 1.2 | 0.8
Generalized abdominal pain | 1.2 | 1.0

Discontinuations due to drug-related adverse events occurred in 2.1% of linezolid-treated and 1.7% of comparator-treated patients. The most common reported drug-related adverse events leading to discontinuation of treatment were nausea, headache, diarrhea, and vomiting.

Pediatric Patients

The safety of linezolid formulations was evaluated in 215 pediatric patients ranging in age from birth through 11 years, and in 248 pediatric patients aged 5 through 17 years (146 of these 248 were age 5 through 11 and 102 were age 12 to 17). These patients were enrolled in two Phase 3 comparator-controlled clinical trials and were treated for up to 28 days. In the study of hospitalized pediatric patients (birth through 11 years) with Gram-positive infections, who were randomized 2 to 1 (linezolid: vancomycin), mortality was 6.0% (13/215) in the linezolid arm and 3.0% (3/101) in the vancomycin arm. However, given the severe underlying illness in the patient population, no causality could be established.

For all indications, 18.8% of linezolid-treated and 34.3% of comparator-treated patients experienced at least one drug-related adverse event.

Table 3 shows the incidence of all-causality, treatment-emergent adverse reactions reported in more than 1% of pediatric patients (and more than 1 patient) in either treatment group in the comparator-controlled Phase 3 trials.

Table 3. Incidence (%) of Treatment-Emergent Adverse Reactions Occurring in greater than 1% of Pediatric Patients (and greater than 1 Patient) in Either Treatment Group in Comparator-Controlled Clinical Trials [Patients from birth through 11 years of age received linezolid 10 mg/kg intravenously and/or by mouth every 8 hours or vancomycin 10 to 15 mg/kg intravenously every 6–24 hours, depending on age and renal clearance.]
ADVERSE REACTIONS | Linezolid (n = 215) | Vancomycin (n = 101)
Diarrhea | 10.8 | 12.1
Vomiting | 9.4 | 9.1
Headache | 0.9 | 0
Anemia | 5.6 | 7.1
Thrombocytopenia | 4.7 | 2.0
Nausea | 1.9 | 0
Generalized abdominal pain | 0.9 | 2.0
Localized abdominal pain | 0.5 | 1.0
Loose stools | 2.3 | 3.0
Eosinophilia | 1.9 | 1.0
Pruritus at non-application site | 1.4 | 2.0
Vertigo | 0 | 0

For all indications, discontinuations due to drug-related adverse events occurred in 0.9% of linezolid-treated and 6.1% of comparator-treated patients.

Laboratory Abnormalities

Linezolid has been associated with thrombocytopenia when used in doses up to and including 600 mg every 12 hours for up to 28 days. In Phase 3 comparator-controlled trials, the percentage of adult patients who developed a substantially low platelet count (defined as less than 75% of lower limit of normal and/or baseline) was 2.4% (range among studies: 0.3 to 10.0%) with linezolid and 1.5% (range among studies: 0.4 to 7.0%) with a comparator. In a study of hospitalized pediatric patients ranging in age from birth through 11 years, the percentage of patients who developed a substantially low platelet count (defined as less than 75% of lower limit of normal and/or baseline) was 12.9% with linezolid and 13.4% with vancomycin. In an outpatient study of pediatric patients aged from 5 through 17 years, the percentage of patients who developed a substantially low platelet count was 0% with linezolid and 0.4% with cefadroxil. Thrombocytopenia associated with the use of linezolid appears to be dependent on duration of therapy (generally greater than 2 weeks of treatment). The platelet counts for most patients returned to the normal range/baseline during the follow-up period. No related clinical adverse events were identified in Phase 3 clinical trials in patients developing thrombocytopenia. Bleeding events were identified in thrombocytopenic patients in a compassionate use program for linezolid; the role of linezolid in these events cannot be determined [see Warnings and Precautions (5.1)].

Changes seen in other laboratory parameters, without regard to drug relationship, revealed no substantial differences between linezolid and the comparators. These changes were generally not clinically significant, did not lead to discontinuation of therapy, and were reversible. The incidence of adult and pediatric patients with at least one substantially abnormal hematologic or serum chemistry value is presented in Tables 4, 5, 6, and 7.

Table 4. Percent of Adult Patients who Experienced at Least One Substantially Abnormal [Less than 75% (less than 50% for neutrophils) of Lower Limit of Normal (LLN) for values normal at baseline; less than 75% (less than 50% for neutrophils) of LLN and of baseline for values abnormal at baseline.] Hematology Laboratory Value in Comparator-Controlled Clinical Trials with Linezolid
Laboratory Assay | Linezolid 600 mg every 12 hours | All Other Comparators [Comparators included cefpodoxime proxetil 200 mg by mouth every 12 hours; ceftriaxone 1 g intravenously every 12 hours; dicloxacillin 500 mg by mouth every 6 hours; oxacillin 2 g intravenously every 6 hours; vancomycin 1 g intravenously every 12 hours.]
Hemoglobin (g/dL) | 7.1 | 6.6
Platelet count (× 10^3/mm^3) | 3.0 | 1.8
WBC (× 10^3/mm^3) | 2.2 | 1.3
Neutrophils (× 10^3/mm^3) | 1.1 | 1.2

Table 5. Percent of Adult Patients who Experienced at Least One Substantially Abnormal [Greater than 2× Upper Limit of Normal (ULN) for values normal at baseline; greater than 2× ULN and greater than 2× baseline for values abnormal at baseline.] Serum Chemistry Laboratory Value in Comparator-Controlled Clinical Trials with Linezolid
Laboratory Assay | Linezolid 600 mg every 12 hours | All Other Comparators [Comparators included cefpodoxime proxetil 200 mg by mouth every 12 hours; ceftriaxone 1 g intravenously every 12 hours; dicloxacillin 500 mg by mouth every 6 hours; oxacillin 2 g intravenously every 6 hours; vancomycin 1 g intravenously every 12 hours.]
AST (U/L) | 5.0 | 6.8
ALT (U/L) | 9.6 | 9.3
LDH (U/L) | 1.8 | 1.5
Alkaline phosphatase (U/L) | 3.5 | 3.1
Lipase (U/L) | 4.3 | 4.2
Amylase (U/L) | 2.4 | 2.0
Total bilirubin (mg/dL) | 0.9 | 1.1
BUN (mg/dL) | 2.1 | 1.5
Creatinine (mg/dL) | 0.2 | 0.6

Table 6. Percent of Pediatric Patients who Experienced at Least One Substantially Abnormal [Less than 75% (less than 50% for neutrophils) of Lower Limit of Normal (LLN) for values normal at baseline; less than 75% (less than 50% for neutrophils) of LLN and less than 75% (less than 50% for neutrophils, less than 90% for hemoglobin if baseline less than LLN) of baseline for values abnormal at baseline.] Hematology Laboratory Value in Comparator-Controlled Clinical Trials with Linezolid [Patients from birth through 11 years of age received linezolid 10 mg/kg intravenously and/or by mouth every 8 hours or vancomycin 10 to 15 mg/kg intravenously every 6–24 hours, depending on age and renal clearance.]
Laboratory Assay | Linezolid | Vancomycin
Hemoglobin (g/dL) | 15.7 | 12.4
Platelet count (× 10^3/mm^3) | 12.9 | 13.4
WBC (× 10^3/mm^3) | 12.4 | 10.3
Neutrophils (× 10^3/mm^3) | 5.9 | 4.3

Table 7. Percent of Pediatric Patients who Experienced at Least One Substantially Abnormal [Greater than 2 × Upper Limit of Normal (ULN) for values normal at baseline; greater than 2× ULN and greater than 2 (greater than 1.5 for total bilirubin) × baseline for values abnormal at baseline.] Serum Chemistry Laboratory Value in Comparator-Controlled Clinical Trials with Linezolid [Patients from birth through 11 years of age received linezolid 10 mg/kg intravenously and/or by mouth every 8 hours or vancomycin 10 to 15 mg/kg intravenously every 6–24 hours, depending on age and renal clearance.]
Laboratory Assay | Linezolid | Vancomycin
ALT (U/L) | 10.1 | 12.5
Lipase (U/L) | --- | ---
Amylase (U/L) | 0.6 | 1.3
Total bilirubin (mg/dL) | 6.3 | 5.2
Creatinine (mg/dL) | 2.4 | 1.0

6.2 Postmarketing Experience

The following adverse reactions have been identified during post-approval use of linezolid. Because these reactions are reported voluntarily from a population of uncertain size, it is not always possible to reliably estimate their frequency or establish a causal relationship to drug exposure:

- Anaphylaxis, angioedema, bullous skin disorders including severe cutaneous adverse reactions (SCAR) such as toxic epidermal necrolysis and Stevens-Johnson syndrome, and hypersensitivity vasculitis.
- Myelosuppression (including anemia, leukopenia, pancytopenia, and thrombocytopenia). Thrombocytopenia has been reported more often in patients with severe renal impairment and in patients with moderate to severe hepatic impairment [see Warnings and Precautions (5.1)]; sideroblastic anemia.
- Peripheral neuropathy, and optic neuropathy sometimes progressing to loss of vision [see Warnings and Precautions (5.2)].
- Serotonin syndrome has been reported in patients receiving concomitant serotonergic agents, including antidepressants such as selective serotonin reuptake inhibitors (SSRIs) and opioids, and linezolid [see Warnings and Precautions (5.3)].
- Lactic acidosis [see Warnings and Precautions (5.7)]. Although these reports have primarily been in patients treated for longer than the maximum recommended duration of 28 days, these events have also been reported in patients receiving shorter courses of therapy.
- Convulsions [see Warnings and Precautions (5.8)].
- Rhabdomyolysis [see Warnings and Precautions (5.9)].
- Hypoglycemia, including symptomatic episodes [see Warnings and Precautions (5.10)].
- Hyponatremia and/or Syndrome of Inappropriate Antidiuretic Hormone Secretion (SIADH) [see Warnings and Precautions (5.11)].
- Superficial tooth discoloration and tongue discoloration have been reported with the use of linezolid. The tooth discoloration was removable with professional dental cleaning (manual descaling) in cases with known outcome.

7 DRUG INTERACTIONS

7.1 Monoamine Oxidase Inhibitors

Linezolid is a reversible, nonselective inhibitor of monoamine oxidase [see Contraindications (4.2) and Clinical Pharmacology (12.3)].

7.2 Adrenergic and Serotonergic Agents

Linezolid has the potential for interaction with adrenergic and serotonergic agents [see Warnings and Precautions (5.3, 5.6) and Clinical Pharmacology (12.3)].

8 USE IN SPECIFIC POPULATIONS

8.1 Pregnancy

Risk Summary

Available data from published and postmarketing case reports with linezolid use in pregnant women have not identified a drug-associated risk of major birth defects, miscarriage, or adverse maternal or fetal outcomes. When administered during organogenesis, linezolid did not cause malformations in mice, rats, or rabbits at maternal exposure levels approximately 6.5 times (mice), equivalent to (rats), or 0.06 times (rabbits) the clinical therapeutic exposure, based on AUCs. However, embryo-fetal lethality was observed in mice at 6.5 times the estimated human exposure. When female rats were dosed during organogenesis through lactation, postnatal survival of pups was decreased at doses approximately equivalent to the estimated human exposure based on AUCs (see Data).

The background risk of major birth defects and miscarriage for the indicated populations is unknown. All pregnancies have a background risk of birth defect, loss, or other adverse outcomes. In the U.S. general population, the estimated background risk of major birth defects and miscarriage in clinically recognized pregnancies is 2 to 4% and 15 to 20%, respectively.

Data

Animal Data

In mice, embryo-fetal toxicities were observed only at doses that caused maternal toxicity (clinical signs and reduced body weight gain). An oral dose of 450 mg/kg/day given from Gestation Day (GD) 6–16 (6.5 times the estimated human exposure based on AUCs) correlated with increased postimplantational embryo death, including total litter loss, decreased fetal body weights, and an increased incidence of costal cartilage fusion. Neither maternal nor embryo-fetal toxicities were observed at doses up to 150 mg/kg/day. Fetal malformations were not observed.

In rats, fetal toxicity was observed at 15 and 50 mg/kg/day administered orally from GD 6–17 (exposures 0.22 times to approximately equivalent to the estimated human exposure, respectively, based on AUCs). The effects consisted of decreased fetal body weights and reduced ossification of sternebrae, a finding often seen in association with decreased fetal body weights. Fetal malformations were not observed. Maternal toxicity, in the form of reduced body weight gain, was seen at 50 mg/kg/day.

In rabbits, reduced fetal body weight occurred only in the presence of maternal toxicity (clinical signs, reduced body weight gain and food consumption) when administered at an oral dose of 15 mg/kg/day given from GD 6–20 (0.06 times the estimated human exposure based on AUCs). Fetal malformations were not observed.

When female rats were treated with 50 mg/kg/day (approximately equivalent to the estimated human exposure based on AUCs) of linezolid during pregnancy and lactation (GD 6 through Lactation Day 20), survival of pups was decreased on postnatal days 1 to 4. Male and female pups permitted to mature to reproductive age, when mated, showed an increase in preimplantation loss.

8.2 Lactation

Risk Summary

Linezolid is present in breast milk. Based on data from available published case reports, the daily dose of linezolid that the infant would receive from breastmilk would be approximately 6% to 9% of the recommended therapeutic infant dose (10 mg/kg every 8 hours). There is no information on the effects of linezolid on the breastfed infant; however, diarrhea and vomiting were the most common adverse reactions reported in clinical trials in infants receiving linezolid therapeutically [see Adverse Reactions (6.1)] and (see Clinical Considerations). There is no information on the effects of linezolid on milk production.

The developmental and health benefits of breastfeeding should be considered along with the mother's clinical need for linezolid and any potential adverse effects on the breastfed child from linezolid or from the underlying maternal condition.

Clinical Considerations

Advise lactating women to monitor a breastfed infant for diarrhea and vomiting.

8.3 Females and Males of Reproductive Potential

Infertility

Males

Based on findings from studies in rats, linezolid may reversibly impair fertility in male patients [see Nonclinical Toxicology (13.1)].

8.4 Pediatric Use

The safety and effectiveness of linezolid for the treatment of pediatric patients with the following infections are supported by evidence from adequate and well-controlled studies in adults, pharmacokinetic data in pediatric patients, and additional data from a comparator-controlled study of Gram-positive infections in pediatric patients ranging in age from birth through 11 years [see Indications and Usage (1), Clinical Pharmacology (12.3) and Clinical Studies (14)]:

- nosocomial pneumonia
- complicated skin and skin structure infections
- community-acquired pneumonia (also supported by evidence from an uncontrolled study in patients ranging in age from 8 months through 12 years)
- vancomycin-resistant Enterococcus faecium infections

Linezolid injection in a single-dose container should be used only in pediatric patients who require the entire 600 mg dose and not any fraction thereof.

Pharmacokinetic information generated in pediatric patients with ventriculoperitoneal shunts showed variable cerebrospinal fluid (CSF) linezolid concentrations following single and multiple dosing of linezolid; therapeutic concentrations were not consistently achieved or maintained in the CSF. Therefore, the use of linezolid for the empiric treatment of pediatric patients with central nervous system infections is not recommended.

The pharmacokinetics of linezolid have been evaluated in pediatric patients from birth to 17 years of age. In general, weight-based clearance of linezolid gradually decreases with increasing age of pediatric patients. However, in preterm (gestational age <34 weeks) neonates <7 days of age, linezolid clearance is often lower than in full-term neonates <7 days of age. Consequently, preterm neonates <7 days of age may need an alternative linezolid dosing regimen of 10 mg/kg every 12 hours [see Dosage and Administration (2.1) and Clinical Pharmacology (12.3)].

In limited clinical experience, 5 out of 6 (83%) pediatric patients with infections due to Gram-positive pathogens with minimum inhibitory concentrations (MICs) of 4 mcg/mL treated with linezolid had clinical cures. However, pediatric patients exhibit wider variability in linezolid clearance and systemic exposure (AUC) compared with adults. In pediatric patients with a sub-optimal clinical response, particularly those with pathogens with MIC of 4 mcg/mL, lower systemic exposure, site and severity of infection, and the underlying medical condition should be considered when assessing clinical response [see Clinical Pharmacology (12.3) and Dosage and Administration (2)].

8.5 Geriatric Use

Of the 2,046 patients treated with linezolid in Phase 3 comparator-controlled clinical trials, 589 (29%) were 65 years or older and 253 (12%) were 75 years or older. No overall differences in safety or effectiveness were observed between these patients and younger patients, and other reported clinical experience has not identified differences in responses between the elderly and younger patients, but greater sensitivity of some older individuals cannot be ruled out.

10 OVERDOSAGE

In the event of overdosage, supportive care is advised, with maintenance of glomerular filtration. Hemodialysis may facilitate more rapid elimination of linezolid. In a Phase 1 clinical trial, approximately 30% of a dose of linezolid was removed during a 3-hour hemodialysis session beginning 3 hours after the dose of linezolid was administered. Data are not available for removal of linezolid with peritoneal dialysis or hemoperfusion. Clinical signs of acute toxicity in animals were decreased activity and ataxia in rats and vomiting and tremors in dogs treated with 3,000 mg/kg/day and 2,000 mg/kg/day, respectively.

11 DESCRIPTION

Linezolid injection contains linezolid, which is a synthetic antibacterial agent of the oxazolidinone class. The chemical name for linezolid is (S)-N-[[3-[3-Fluoro-4-(4-morpholinyl)phenyl]-2-oxo-5-oxazolidinyl] methyl]-acetamide.

The empirical formula is C16H20FN3O4. Its molecular weight is 337.35, and its chemical structure is represented below:

Linezolid injection is supplied as a ready-to-use sterile isotonic solution for intravenous infusion. Each container contains 600 mg of linezolid in 300 mL of a clear, colorless to slightly yellow aqueous solution. Inactive ingredients include: citric acid anhydrous USP 1.92 mg/mL, sodium chloride USP 9 mg/mL, sodium hydroxide NF 0.76 mg/mL, and water for injection USP. Sodium hydroxide NF and/or hydrochloric acid NF are used to adjust the pH. The sodium (Na^+) content is 3.98 mg/mL (52 mEq/300 mL container).

12 CLINICAL PHARMACOLOGY

12.1 Mechanism of Action

Linezolid is an antibacterial drug [see Microbiology (12.4)].

12.2 Pharmacodynamics

In a randomized, positive- and placebo-controlled crossover thorough QT study, 40 healthy subjects were administered a single linezolid 600 mg dose via a 1 hour IV infusion, a single linezolid 1,200 mg dose via a 1 hour IV infusion, placebo, and a single oral dose of positive control. At both the 600 mg and 1,200 mg linezolid doses, no significant effect on QTc interval was detected at peak plasma concentration or at any other time.

12.3 Pharmacokinetics

The mean pharmacokinetic parameters of linezolid in adults after single and multiple oral and intravenous doses are summarized in Table 8. Plasma concentrations of linezolid at steady-state after oral doses of 600 mg given every 12 hours are shown in Figure 1.

Table 8. Mean (Standard Deviation) Pharmacokinetic Parameters of Linezolid in Adults
Dose of Linezolid | Cmax mcg/mL | Cmin mcg/mL | Tmax hrs | AUC [AUC for single dose = AUC0–∞; for multiple dose = AUC0–τ] mcg∙h/mL | t1/2 hrs | CL mL/min
400 mg tablet
single dose [Data dose-normalized from 375 mg] | 8.10 (1.83) | --- | 1.52 (1.01) | 55.10 (25.00) | 5.20 (1.50) | 146 (67)
every 12 hours | 11.00 (4.37) | 3.08 (2.25) | 1.12 (0.47) | 73.40 (33.50) | 4.69 (1.70) | 110 (49)
600 mg tablet
single dose | 12.70 (3.96) | --- | 1.28 (0.66) | 91.40 (39.30) | 4.26 (1.65) | 127 (48)
every 12 hours | 21.20 (5.78) | 6.15 (2.94) | 1.03 (0.62) | 138.00 (42.10) | 5.40 (2.06) | 80 (29)
600 mg IV injection [Data dose-normalized from 625 mg, intravenous dose was given as 0.5-hour infusion. Cmax = Maximum plasma concentration; Cmin = Minimum plasma concentration; Tmax = Time to Cmax; AUC = Area under concentration-time curve; t1/2 = Elimination half-life; CL = Systemic clearance]
single dose | 12.90 (1.60) | --- | 0.50 (0.10) | 80.20 (33.30) | 4.40 (2.40) | 138 (39)
every 12 hours | 15.10 (2.52) | 3.68 (2.36) | 0.51 (0.03) | 89.70 (31.00) | 4.80 (1.70) | 123 (40)
600 mg oral suspension
single dose | 11.00 (2.76) | --- | 0.97 (0.88) | 80.80 (35.10) | 4.60 (1.71) | 141 (45)

Figure 1. Plasma Concentrations of Linezolid in Adults at Steady-State Following Oral Dosing Every 12 Hours (Mean ± Standard Deviation, n=16)

Absorption

Linezolid is extensively absorbed after oral dosing. Maximum plasma concentrations are reached approximately 1 to 2 hours after dosing, and the absolute bioavailability is approximately 100%. Therefore, linezolid may be given orally or intravenously without dose adjustment.

Linezolid may be administered without regard to the timing of meals. The time to reach the maximum concentration is delayed from 1.5 hours to 2.2 hours and Cmax is decreased by about 17% when high fat food is given with linezolid. However, the total exposure measured as AUC0–∞ is similar under both conditions.

Distribution

Animal and human pharmacokinetic studies have demonstrated that linezolid readily distributes to well-perfused tissues. The plasma protein binding of linezolid is approximately 31% and is concentration-independent. The volume of distribution of linezolid at steady-state averaged 40 to 50 liters in healthy adult volunteers.

Linezolid concentrations have been determined in various fluids from a limited number of subjects in Phase 1 volunteer studies following multiple dosing of linezolid. The ratio of linezolid in saliva relative to plasma was 1.2 to 1 and the ratio of linezolid in sweat relative to plasma was 0.55 to 1.

Metabolism

Linezolid is primarily metabolized by oxidation of the morpholine ring, which results in two inactive ring-opened carboxylic acid metabolites: the aminoethoxyacetic acid metabolite (A), and the hydroxyethyl glycine metabolite (B). Formation of metabolite A is presumed to be formed via an enzymatic pathway whereas metabolite B is mediated by a non-enzymatic chemical oxidation mechanism in vitro. In vitro studies have demonstrated that linezolid is minimally metabolized and may be mediated by human cytochrome P450. However, the metabolic pathway of linezolid is not fully understood.

Excretion

Nonrenal clearance accounts for approximately 65% of the total clearance of linezolid. Under steady-state conditions, approximately 30% of the dose appears in the urine as linezolid, 40% as metabolite B, and 10% as metabolite A. The mean renal clearance of linezolid is 40 mL/min which suggests net tubular reabsorption. Virtually no linezolid appears in the feces, while approximately 6% of the dose appears in the feces as metabolite B, and 3% as metabolite A.

A small degree of nonlinearity in clearance was observed with increasing doses of linezolid, which appears to be due to lower renal and nonrenal clearance of linezolid at higher concentrations. However, the difference in clearance was small and was not reflected in the apparent elimination half-life.

Specific Populations

Geriatric Patients

The pharmacokinetics of linezolid are not significantly altered in elderly patients (65 years or older). Therefore, dose adjustment for geriatric patients is not necessary.

Pediatric Patients

The pharmacokinetics of linezolid following a single intravenous dose were investigated in pediatric patients ranging in age from birth through 17 years (including premature and full-term neonates), in healthy adolescent subjects ranging in age from 12 through 17 years, and in pediatric patients ranging in age from 1 week through 12 years. The pharmacokinetic parameters of linezolid are summarized in Table 9 for the pediatric populations studied and healthy adult subjects after administration of single intravenous doses.

The Cmax and the volume of distribution (Vss) of linezolid are similar regardless of age in pediatric patients. However, plasma clearance of linezolid varies as a function of age. With the exclusion of pre-term neonates less than one week of age, weight-based clearance is most rapid in the youngest age groups ranging from <1 week old to 11 years, resulting in lower single-dose systemic exposure (AUC) and a shorter half-life as compared with adults. As the age of pediatric patients increases, the weight-based clearance of linezolid gradually decreases, and by adolescence mean clearance values approach those observed for the adult population. There is increased inter-subject variability in linezolid clearance and systemic drug exposure (AUC) across all pediatric age groups as compared with adults.

Similar mean daily AUC values were observed in pediatric patients from birth to 11 years of age dosed every 8 hours relative to adolescents or adults dosed every 12 hours. Therefore, the dosage for pediatric patients up to 11 years of age should be 10 mg/kg every 8 hours. Pediatric patients 12 years and older should receive 600 mg every 12 hours [see Dosage and Administration (2)].

Table 9. Pharmacokinetic Parameters of Linezolid in Pediatrics and Adults Following a Single Intravenous Infusion of 10 mg/kg or 600 mg Linezolid (Mean: (%CV); [Min, Max Values])
Age Group | Cmax mcg/mL | Vss L/kg | AUC [AUC = Single dose AUC0–∞] mcg∙h/mL | t1/2 Hrs | CL mL/min/kg
Neonatal Patients
Pre-term [In this data set, "pre-term" is defined as less than 34 weeks gestational age (Note: Only 1 patient enrolled was pre-term with a postnatal age between 1 week and 28 days)] | 12.7 (30%) | 0.81 (24%) | 108 (47%) | 5.6 (46%) | 2.0 (52%)
<1 week (N = 9) [Dose of 10 mg/kg] | [9.6, 22.2] | [0.43, 1.05] | [41, 191] | [2.4, 9.8] | [0.9, 4.0]
Full-term [In this data set, "full-term" is defined as greater than or equal to 34 weeks gestational age] | 11.5 (24%) | 0.78 (20%) | 55 (47%) | 3.0 (55%) | 3.8 (55%)
<1 week (N = 10) | [8.0, 18.3] | [0.45, 0.96] | [19, 103] | [1.3, 6.1] | [1.5, 8.8]
Full-term | 12.9 (28%) | 0.66 (29%) | 34 (21%) | 1.5 (17%) | 5.1 (22%)
≥1 week to ≤28 days (N = 10) | [7.7, 21.6] | [0.35, 1.06] | [23, 50] | [1.2, 1.9] | [3.3, 7.2]
Infant Patients
>28 days to <3 Months | 11.0 (27%) | 0.79 (26%) | 33 (26%) | 1.8 (28%) | 5.4 (32%)
(N = 12) | [7.2, 18.0] | [0.42, 1.08] | [17, 48] | [1.2, 2.8] | [3.5, 9.9]
Pediatric Patients
3 months through 11 years | 15.1 (30%) | 0.69 (28%) | 58 (54%) | 2.9 (53%) | 3.8 (53%)
(N = 59) | [6.8, 36.7] | [0.31, 1.50] | [19, 153] | [0.9, 8.0] | [1.0, 8.5]
Adolescent Subjects and Patients
12 through 17 years [Dose of 600 mg or 10 mg/kg up to a maximum of 600 mg] | 16.7 (24%) | 0.61 (15%) | 95 (44%) | 4.1 (46%) | 2.1 (53%)
(N = 36) | [9.9, 28.9] | [0.44, 0.79] | [32, 178] | [1.3, 8.1] | [0.9, 5.2]
Adult Subjects [Dose normalized to 600 mg] | [8.2, 19.3] | [0.45, 0.84] | [53, 155] | [1.8, 8.3] | [0.9, 3.3]
(N = 29) | 12.5 (21%) | 0.65 (16%) | 91 (33%) | 4.9 (35%) | 1.7 (34%)
Cmax = Maximum plasma concentration; Vss = Volume of distribution; AUC = Area under concentration-time curve; t1/2 = Apparent elimination half-life; CL = Systemic clearance normalized for body weight

Gender

Females have a slightly lower volume of distribution of linezolid than males. Plasma concentrations are higher in females than in males, which is partly due to body weight differences. After a 600-mg dose, mean oral clearance is approximately 38% lower in females than in males. However, there are no significant gender differences in mean apparent elimination-rate constant or half-life. Thus, drug exposure in females is not expected to substantially increase beyond levels known to be well tolerated. Therefore, dose adjustment by gender does not appear to be necessary.

Renal Impairment

The pharmacokinetics of the parent drug, linezolid, are not altered in patients with any degree of renal impairment; however, the two primary metabolites of linezolid accumulate in patients with renal impairment, with the amount of accumulation increasing with the severity of renal dysfunction (see Table 10). The pharmacokinetics of linezolid and its two metabolites have also been studied in patients with end-stage renal disease (ESRD) receiving hemodialysis. In the ESRD study, 14 patients were dosed with linezolid 600 mg every 12 hours for 14.5 days (see Table 11). Because similar plasma concentrations of linezolid are achieved regardless of renal function, no dose adjustment is recommended for patients with renal impairment. However, given the absence of information on the clinical significance of accumulation of the primary metabolites, use of linezolid in patients with renal impairment should be weighed against the potential risks of accumulation of these metabolites. Both linezolid and the two metabolites are eliminated by hemodialysis. No information is available on the effect of peritoneal dialysis on the pharmacokinetics of linezolid. Approximately 30% of a dose was eliminated in a 3-hour hemodialysis session beginning 3 hours after the dose of linezolid was administered; therefore, linezolid should be given after hemodialysis.

Table 10. Mean (Standard Deviation) AUCs and Elimination Half-lives of Linezolid and Metabolites A and B in Patients with Varying Degrees of Renal Impairment After a Single 600 mg Oral Dose of Linezolid
Parameter | Healthy Subjects CLCR >80 mL/min | Moderate Renal Impairment 30< CLCR <80 mL/min | Severe Renal Impairment 10< CLCR <30 mL/min
LINEZOLID
AUC0–∞, mcg h/mL | 110 (22) | 128 (53) | 127 (66)
t1/2, hours | 6.4 (2.2) | 6.1 (1.7) | 7.1 (3.7)
METABOLITE A
AUC0–48, mcg h/mL | 7.6 (1.9) | 11.7 (4.3) | 56.5 (30.6)
t1/2, hours | 6.3 (2.1) | 6.6 (2.3) | 9.0 (4.6)
METABOLITE B [Metabolite B is the major metabolite of linezolid.]
AUC0–48, mcg h/mL | 30.5 (6.2) | 51.1 (38.5) | 203 (92)
t1/2, hours | 6.6 (2.7) | 9.9 (7.4) | 11.0 (3.9)

Table 11. Mean (Standard Deviation) AUCs and Elimination Half-lives of Linezolid and Metabolites A and B in Subjects with End-Stage Renal Disease (ESRD) After the Administration of 600 mg Linezolid Every 12 Hours for 14.5 Days
Parameter | ESRD Subjects [between hemodialysis sessions]
LINEZOLID
AUC0–12, mcg h/mL (after last dose) | 181 (52.3)
t1/2, h (after last dose) | 8.3 (2.4)
METABOLITE A
AUC0–12, mcg h/mL (after last dose) | 153 (40.6)
t1/2, h (after last dose) | 15.9 (8.5)
METABOLITE B [Metabolite B is the major metabolite of linezolid.]
AUC0–12, mcg h/mL (after last dose) | 356 (99.7)
t1/2, h (after last dose) | 34.8 (23.1)

Hepatic Impairment

The pharmacokinetics of linezolid are not altered in patients (n = 7) with mild-to-moderate hepatic impairment (Child-Pugh class A or B). On the basis of the available information, no dose adjustment is recommended for patients with mild-to-moderate hepatic impairment. The pharmacokinetics of linezolid in patients with severe hepatic impairment have not been evaluated.

Drug Interactions

Drugs Metabolized by Cytochrome P450

Linezolid is not an inducer of cytochrome P450 (CYP450) in rats. In addition, linezolid does not inhibit the activities of clinically significant human CYP isoforms (e.g., 1A2, 2C9, 2C19, 2D6, 2E1, 3A4). Therefore, linezolid is not expected to affect the pharmacokinetics of other drugs metabolized by these major enzymes. Concurrent administration of linezolid does not substantially alter the pharmacokinetic characteristics of (S)-warfarin, which is extensively metabolized by CYP2C9. Drugs such as warfarin and phenytoin, which are CYP2C9 substrates, may be given with linezolid without changes in dosage regimen.

Antibacterial Drugs

Aztreonam: The pharmacokinetics of linezolid or aztreonam are not altered when administered together.

Gentamicin: The pharmacokinetics of linezolid or gentamicin are not altered when administered together.

Antioxidants

The potential for drug-drug interactions with linezolid and the antioxidants Vitamin C and Vitamin E was studied in healthy volunteers. Subjects were administered a 600 mg oral dose of linezolid on Day 1, and another 600 mg dose of linezolid on Day 8. On Days 2–9, subjects were given either Vitamin C (1,000 mg/day) or Vitamin E (800 IU/ day). The AUC0–∞ of linezolid increased 2.3% when co-administered with Vitamin C and 10.9% when co-administered with Vitamin E. No linezolid dose adjustment is recommended during co-administration with Vitamin C or Vitamin E.

Strong CYP 3A4 Inducers

Rifampin: The effect of rifampin on the pharmacokinetics of linezolid was evaluated in a study of 16 healthy adult males. Volunteers were administered oral linezolid 600 mg twice daily for 5 doses with and without rifampin 600 mg once daily for 8 days. Co-administration of rifampin with linezolid resulted in a 21% decrease in linezolid Cmax [90% CI, 15% – 27%] and a 32% decrease in linezolid AUC0–12 [90% CI, 27% – 37%]. The clinical significance of this interaction is unknown. The mechanism of this interaction is not fully understood and may be related to the induction of hepatic enzymes. Other strong inducers of hepatic enzymes (e.g. carbamazepine, phenytoin, phenobarbital) could cause a similar or smaller decrease in linezolid exposure.

Monoamine Oxidase Inhibition

Linezolid is a reversible, nonselective inhibitor of monoamine oxidase. Therefore, linezolid has the potential for interaction with adrenergic and serotonergic agents.

Adrenergic Agents

Some individuals receiving linezolid may experience a reversible enhancement of the pressor response to indirect-acting sympathomimetic agents, vasopressor or dopaminergic agents. Commonly used drugs such as pseudoephedrine have been specifically studied. Initial doses of adrenergic agents, such as dopamine or epinephrine, should be reduced and titrated to achieve the desired response.

Tyramine: A significant pressor response has been observed in normal adult subjects receiving linezolid and tyramine doses of more than 100 mg. Therefore, patients receiving linezolid need to avoid consuming large amounts of foods or beverages with high tyramine content [see Patient Counseling Information (17)].

Pseudoephedrine HCl: A reversible enhancement of the pressor response of pseudoephedrine HCl (PSE) is observed when linezolid is administered to healthy normotensive subjects [see Warnings and Precautions (5.6) and Drug Interactions (7)]. A similar study has not been conducted in hypertensive patients. The interaction studies conducted in normotensive subjects evaluated the blood pressure and heart rate effects of placebo, phenylpropanolamine (PPA) or PSE alone, linezolid alone, and the combination of steady-state linezolid (600 mg every 12 hours for 3 days) with two doses of PPA (25 mg) or PSE (60 mg) given 4 hours apart. Heart rate was not affected by any of the treatments. Blood pressure was increased with both combination treatments. Maximum blood pressure levels were seen 2 to 3 hours after the second dose of PPA or PSE, and returned to baseline 2 to 3 hours after peak. The results of the PPA study follow, showing the mean (and range) maximum systolic blood pressure in mm Hg: placebo = 121 (103 to 158); linezolid alone = 120 (107 to 135); PPA alone = 125 (106 to 139); PPA with linezolid = 147 (129 to 176). The results from the PSE study were similar to those in the PPA study. The mean maximum increase in systolic blood pressure over baseline was 32 mm Hg (range: 20–52 mm Hg) and 38 mm Hg (range: 18–79 mm Hg) during co-administration of linezolid with pseudoephedrine or phenylpropanolamine, respectively.

Serotonergic Agents

Dextromethorphan: The potential drug-drug interaction with dextromethorphan was studied in healthy volunteers. Subjects were administered dextromethorphan (two 20-mg doses given 4 hours apart) with or without linezolid.

No serotonin syndrome effects (confusion, delirium, restlessness, tremors, blushing, diaphoresis, hyperpyrexia) have been observed in normal subjects receiving linezolid and dextromethorphan.

12.4 Microbiology

Mechanism of Action

Linezolid is a synthetic antibacterial agent of the oxazolidinone class, which has clinical utility in the treatment of infections caused by aerobic Gram-positive bacteria. The in vitro spectrum of activity of linezolid also includes certain Gram-negative bacteria and anaerobic bacteria. Linezolid binds to a site on the bacterial 23S ribosomal RNA of the 50S subunit and prevents the formation of a functional 70S initiation complex, which is essential for bacterial reproduction. The results of time-kill studies have shown linezolid to be bacteriostatic against enterococci and staphylococci. For streptococci, linezolid was found to be bactericidal for the majority of isolates.

Resistance

In vitro studies have shown that point mutations in the 23S rRNA are associated with linezolid resistance. Reports of vancomycin-resistant Enterococcus faecium becoming resistant to linezolid during its clinical use have been published. There are reports of Staphylococcus aureus (methicillin-resistant) developing resistance to linezolid during clinical use. The linezolid resistance in these organisms is associated with a point mutation in the 23S rRNA (substitution of thymine for guanine at position 2576) of the organism. Organisms resistant to oxazolidinones via mutations in chromosomal genes encoding 23S rRNA or ribosomal proteins (L3 and L4) are generally cross-resistant to linezolid. Also linezolid resistance in staphylococci mediated by the enzyme methyltransferase has been reported. This resistance is mediated by the cfr (chloramphenicol-florfenicol) gene located on a plasmid which is transferable between staphylococci.

Interaction with Other Antimicrobial Drugs

In vitro studies have demonstrated additivity or indifference between linezolid and vancomycin, gentamicin, rifampin, imipenem-cilastatin, aztreonam, ampicillin, or streptomycin.

Linezolid has been shown to be active against most isolates of the following microorganisms, both in vitro and in clinical infections [see Indications and Usage (1)].

Gram-positive bacteria

Enterococcus faecium (vancomycin-resistant isolates only)
Staphylococcus aureus (including methicillin-resistant isolates)
Streptococcus agalactiae
Streptococcus pneumoniae
Streptococcus pyogenes

The following in vitro data are available, but their clinical significance is unknown. Greater than 90% of the following bacteria exhibit an in vitro MIC less than or equal to the linezolid-susceptible breakpoint for organisms of similar genus. The safety and effectiveness of linezolid in treating clinical infections due to these bacteria have not been established in adequate and well-controlled clinical trials.

Gram-positive bacteria

Enterococcus faecalis (including vancomycin-resistant isolates)
Enterococcus faecium (vancomycin-susceptible isolates)
Staphylococcus epidermidis (including methicillin-resistant isolates)
Staphylococcus haemolyticus
Viridans group streptococci

Gram-negative bacteria

Pasteurella multocida

Susceptibility Testing

For specific information regarding susceptibility test interpretive criteria and associated test methods and quality control standards recognized by FDA for this drug, please see: https://www.fda.gov/STIC.

13 NONCLINICAL TOXICOLOGY

13.1 Carcinogenesis, Mutagenesis, Impairment of Fertility

Lifetime studies in animals have not been conducted to evaluate the carcinogenic potential of linezolid. Neither mutagenic nor clastogenic potential was found in a battery of tests including: assays for mutagenicity (Ames bacterial reversion and CHO cell mutation), an in vitro unscheduled DNA synthesis (UDS) assay, an in vitro chromosome aberration assay in human lymphocytes, and an in vivo mouse micronucleus assay.

Linezolid did not affect the fertility or reproductive performance of adult female rats given oral doses of up to 100 mg/kg/day for 14 days prior to mating through Gestation Day 7. It reversibly decreased fertility and reproductive performance in adult male rats when given at doses ≥50 mg/kg/day, with exposures approximately equal to or greater than the expected human exposure level (exposure comparisons are based on AUCs). The reversible fertility effects were mediated through altered spermatogenesis. Affected spermatids contained abnormally formed and oriented mitochondria and were non-viable. Epithelial cell hypertrophy and hyperplasia in the epididymis was observed in conjunction with decreased fertility. Similar epididymal changes were not seen in dogs.

In sexually mature male rats exposed to drug as juveniles, mildly decreased fertility was observed following treatment with linezolid through most of their period of sexual development (50 mg/kg/day from days 7 to 36 of age, and 100 mg/kg/day from days 37 to 55 of age), with exposures up to 1.7 times greater than mean AUCs observed in pediatric patients aged 3 months to 11 years. Decreased fertility was not observed with shorter treatment periods, corresponding to exposure in utero through the early neonatal period (gestation day 6 through postnatal day 5), neonatal exposure (postnatal days 5 to 21), or to juvenile exposure (postnatal days 22 to 35). Reversible reductions in sperm motility and altered sperm morphology were observed in rats treated from postnatal day 22 to 35.

13.2 Animal Toxicology and/or Pharmacology

Target organs of linezolid toxicity were similar in juvenile and adult rats and dogs. Dose- and time-dependent myelosuppression, as evidenced by bone marrow hypocellularity/decreased hematopoiesis, decreased extramedullary hematopoiesis in spleen and liver, and decreased levels of circulating erythrocytes, leukocytes, and platelets have been seen in animal studies. Lymphoid depletion occurred in thymus, lymph nodes, and spleen. Generally, the lymphoid findings were associated with anorexia, weight loss, and suppression of body weight gain, which may have contributed to the observed effects.

In rats administered linezolid orally for 6 months, non-reversible, minimal to mild axonal degeneration of sciatic nerves was observed at 80 mg/kg/day; minimal degeneration of the sciatic nerve was also observed in 1 male at this dose level at a 3-month interim necropsy. Sensitive morphologic evaluation of perfusion-fixed tissues was conducted to investigate evidence of optic nerve degeneration. Minimal to moderate optic nerve degeneration was evident in 2 male rats after 6 months of dosing, but the direct relationship to drug was equivocal because of the acute nature of the finding and its asymmetrical distribution. The nerve degeneration observed was microscopically comparable to spontaneous unilateral optic nerve degeneration reported in aging rats and may be an exacerbation of common background change.

These effects were observed at exposure levels that are comparable to those observed in some human subjects. The hematopoietic and lymphoid effects were reversible, although in some studies, reversal was incomplete within the duration of the recovery period.

14 CLINICAL STUDIES

14.1 Adults

Nosocomial Pneumonia

Adult patients with clinically and radiologically documented nosocomial pneumonia were enrolled in a randomized, multi-center, double-blind trial. Patients were treated for 7 to 21 days. One group received Linezolid injection 600 mg every 12 hours, and the other group received vancomycin 1 g every 12 hours intravenously. Both groups received concomitant aztreonam (1 to 2 g every 8 hours intravenously), which could be continued if clinically indicated. There were 203 linezolid-treated and 193 vancomycin-treated patients enrolled in the study. One hundred twenty-two (60%) linezolid-treated patients and 103 (53%) vancomycin-treated patients were clinically evaluable. The cure rates in clinically evaluable patients were 57% for linezolid-treated patients and 60% for vancomycin-treated patients. The cure rates in clinically evaluable patients with ventilator-associated pneumonia were 47% for linezolid-treated patients and 40% for vancomycin-treated patients. A modified intent-to-treat (MITT) analysis of 94 linezolid-treated patients and 83 vancomycin-treated patients included subjects who had a pathogen isolated before treatment. The cure rates in the MITT analysis were 57% in linezolid-treated patients and 46% in vancomycin-treated patients. The cure rates by pathogen for microbiologically evaluable patients are presented in Table 12.

Table 12. Cure Rates at the Test-of-Cure Visit for Microbiologically Evaluable Adult Patients with Nosocomial Pneumonia
 | Cured
Pathogen | Linezolid n/N (%) | Vancomycin n/N (%)
Staphylococcus aureus | 23/38 (61) | 14/23 (61)
Methicillin-resistant S. aureus | 13/22 (59) | 7/10 (70)
Streptococcus pneumoniae | 9/9 (100) | 9/10 (90)

Complicated Skin and Skin Structure Infections

Adult patients with clinically documented complicated skin and skin structure infections were enrolled in a randomized, multi-center, double-blind, double-dummy trial comparing study medications administered intravenously followed by medications given orally for a total of 10 to 21 days of treatment. One group of patients received Linezolid injection 600 mg every 12 hours followed by Linezolid Tablets 600 mg every 12 hours; the other group received oxacillin 2 g every 6 hours intravenously followed by dicloxacillin 500 mg every 6 hours orally. Patients could receive concomitant aztreonam if clinically indicated. There were 400 linezolid-treated and 419 oxacillin-treated patients enrolled in the study. Two hundred forty-five (61%) linezolid-treated patients and 242 (58%) oxacillin-treated patients were clinically evaluable. The cure rates in clinically evaluable patients were 90% in linezolid-treated patients and 85% in oxacillin-treated patients. A modified intent-to-treat (MITT) analysis of 316 linezolid-treated patients and 313 oxacillin-treated patients included subjects who met all criteria for study entry. The cure rates in the MITT analysis were 86% in linezolid-treated patients and 82% in oxacillin-treated patients. The cure rates by pathogen for microbiologically evaluable patients are presented in Table 13.

Table 13. Cure Rates at the Test-of-Cure Visit for Microbiologically Evaluable Adult Patients with Complicated Skin and Skin Structure Infections
 | Cured
Pathogen | Linezolid n/N (%) | Oxacillin/Dicloxacillin n/N (%)
Staphylococcus aureus | 73/83 (88) | 72/84 (86)
Methicillin-resistant S. aureus | 2/3 (67) | 0/0 (-)
Streptococcus agalactiae | 6/6 (100) | 3/6 (50)
Streptococcus pyogenes | 18/26 (69) | 21/28 (75)

A separate study provided additional experience with the use of linezolid in the treatment of methicillin-resistant Staphylococcus aureus (MRSA) infections. This was a randomized, open-label trial in hospitalized adult patients with documented or suspected MRSA infection.

One group of patients received Linezolid injection 600 mg every 12 hours followed by Linezolid Tablets 600 mg every 12 hours. The other group of patients received vancomycin 1 g every 12 hours intravenously. Both groups were treated for 7 to 28 days, and could receive concomitant aztreonam or gentamicin if clinically indicated. The cure rates in microbiologically evaluable patients with MRSA skin and skin structure infection were 26/33 (79%) for linezolid-treated patients and 24/33 (73%) for vancomycin-treated patients.

Diabetic Foot Infections

Adult diabetic patients with clinically documented complicated skin and skin structure infections ("diabetic foot infections") were enrolled in a randomized (2:1 ratio), multi-center, open-label trial comparing study medications administered intravenously or orally for a total of 14 to 28 days of treatment. One group of patients received linezolid 600 mg every 12 hours intravenously or orally; the other group received ampicillin/sulbactam 1.5 to 3 g intravenously or amoxicillin/clavulanate 500 to 875 mg every 8 to 12 hours orally. In countries where ampicillin/sulbactam is not marketed, amoxicillin/clavulanate 500 mg to 2 g every 6 hours was used for the intravenous regimen. Patients in the comparator group could also be treated with vancomycin 1 g every 12 hours intravenously if MRSA was isolated from the foot infection. Patients in either treatment group who had Gram-negative bacilli isolated from the infection site could also receive aztreonam 1 to 2 g every 8–12 hours intravenously. All patients were eligible to receive appropriate adjunctive treatment methods, such as debridement and off-loading, as typically required in the treatment of diabetic foot infections, and most patients received these treatments. There were 241 linezolid-treated and 120 comparator-treated patients in the intent-to-treat (ITT) study population. Two hundred twelve (86%) linezolid-treated patients and 105 (85%) comparator-treated patients were clinically evaluable. In the ITT population, the cure rates were 68.5% (165/241) in linezolid-treated patients and 64% (77/120) in comparator-treated patients, where those with indeterminate and missing outcomes were considered failures. The cure rates in the clinically evaluable patients (excluding those with indeterminate and missing outcomes) were 83% (159/192) and 73% (74/101) in the linezolid- and comparator-treated patients, respectively. A critical post-hoc analysis focused on 121 linezolid-treated and 60 comparator-treated patients who had a Gram-positive pathogen isolated from the site of infection or from blood, who had less evidence of underlying osteomyelitis than the overall study population, and who did not receive prohibited antimicrobials. Based upon that analysis, the cure rates were 71% (86/121) in the linezolid-treated patients and 63% (38/60) in the comparator-treated patients. None of the above analyses were adjusted for the use of adjunctive therapies. The cure rates by pathogen for microbiologically evaluable patients are presented in Table 14.

Table 14. Cure Rates at the Test-of-Cure Visit for Microbiologically Evaluable Adult Patients with Diabetic Foot Infections
 | Cured
Pathogen | Linezolid n/N (%) | Comparator n/N (%)
Staphylococcus aureus | 49/63 (78) | 20/29 (69)
Methicillin-resistant S. aureus | 12/17 (71) | 2/3 (67)
Streptococcus agalactiae | 25/29 (86) | 9/16 (56)

Vancomycin-Resistant Enterococcal Infections

Adult patients with documented or suspected vancomycin-resistant enterococcal infection were enrolled in a randomized, multi-center, double-blind trial comparing a high dose of linezolid (600 mg) with a low dose of linezolid (200 mg) given every 12 hours either intravenously (IV) or orally for 7 to 28 days. Patients could receive concomitant aztreonam or aminoglycosides. There were 79 patients randomized to high-dose linezolid and 66 to low-dose linezolid. The intent-to-treat (ITT) population with documented vancomycin-resistant enterococcal infection at baseline consisted of 65 patients in the high-dose arm and 52 in the low-dose arm.

The cure rates for the ITT population with documented vancomycin-resistant enterococcal infection at baseline are presented in Table 15 by source of infection. These cure rates do not include patients with missing or indeterminate outcomes. The cure rate was higher in the high-dose arm than in the low-dose arm, although the difference was not statistically significant at the 0.05 level.

Table 15. Cure Rates at the Test-of-Cure Visit for ITT Adult Patients with Documented Vancomycin-Resistant Enterococcal Infections at Baseline
 | Cured
Source of Infection | Linezolid 600 mg every 12 hours n/N (%) | Linezolid 200 mg every 12 hours n/N (%)
Any site | 39/58 (67) | 24/46 (52)
Any site with associated bacteremia | 10/17 (59) | 4/14 (29)
Bacteremia of unknown origin | 5/10 (50) | 2/7 (29)
Skin and skin structure | 9/13 (69) | 5/5 (100)
Urinary tract | 12/19 (63) | 12/20 (60)
Pneumonia | 2/3 (67) | 0/1 (0)
Other [Includes sources of infection such as hepatic abscess, biliary sepsis, necrotic gall bladder, pericolonic abscess, pancreatitis, and catheter-related infection.] | 11/13 (85) | 5/13 (39)

14.2 Pediatric Patients

Infections due to Gram-positive Bacteria

A safety and efficacy study provided experience on the use of linezolid in pediatric patients for the treatment of nosocomial pneumonia, complicated skin and skin structure infections and other infections due to Gram-positive bacterial pathogens, including methicillin-resistant and -susceptible Staphylococcus aureus and vancomycin-resistant Enterococcus faecium. Pediatric patients ranging in age from birth through 11 years with infections caused by the documented or suspected Gram-positive bacteria were enrolled in a randomized, open-label, comparator-controlled trial. One group of patients received Linezolid injection 10 mg/kg every 8 hours followed by Linezolid for Oral Suspension 10 mg/kg every 8 hours. A second group received vancomycin 10 to 15 mg/kg intravenously every 6 to 24 hours, depending on age and renal clearance. Patients who had confirmed VRE infections were placed in a third arm of the study and received linezolid 10 mg/kg every 8 hours intravenously and/or orally. All patients were treated for a total of 10 to 28 days and could receive concomitant Gram-negative antibacterial drugs if clinically indicated. In the intent-to-treat (ITT) population, there were 206 patients randomized to linezolid and 102 patients randomized to vancomycin. The cure rates for ITT, MITT, and clinically evaluable patients are presented in Table 16. After the study was completed, 13 additional patients ranging from 4 days through 16 years of age were enrolled in an open-label extension of the VRE arm of the study. Table 17 provides clinical cure rates by pathogen for microbiologically evaluable patients including microbiologically evaluable patients with vancomycin-resistant Enterococcus faecium from the extension of this study.

Table 16. Cure Rates at the Test-of-Cure Visit for Intent-to-Treat, Modified Intent-to-Treat, and Clinically Evaluable Pediatric Patients for the Overall Population and by Select Baseline Diagnosis
 | ITT |  | MITT [MITT = ITT patients with an isolated Gram-positive pathogen at baseline] |  | Clinically Evaluable
Population | Linezolid n/N (%) | Vancomycin n/N (%) | Linezolid n/N (%) | Vancomycin n/N (%) | Linezolid n/N (%) | Vancomycin n/N (%)
Any diagnosis | 150/186 (81) | 69/83 (83) | 86/108 (80) | 44/49 (90) | 106/117 (91) | 49/54 (91)
Complicated skin and skin structure infections | 61/72 (85) | 31/34 (91) | 37/43 (86) | 22/23 (96) | 46/49 (94) | 26/27 (96)
Nosocomial pneumonia | 13/18 (72) | 11/12 (92) | 5/6 (83) | 4/4 (100) | 7/7 (100) | 5/5 (100)

Table 17. Cure Rates at the Test-of-Cure Visit for Microbiologically Evaluable Pediatric Patients with Infections due to Gram-positive Pathogens
 | Microbiologically Evaluable
Pathogen | Linezolid n/N (%) | Vancomycin n/N (%)
Vancomycin-resistant Enterococcus faecium | 6/8 (75) [Includes data from 7 patients enrolled in the open-label extension of this study.] | 0/0 (-)
Staphylococcus aureus | 36/38 (95) | 23/24 (96)
Methicillin-resistant S. aureus | 16/17 (94) | 9/9 (100)
Streptococcus pyogenes | 2/2 (100) | 1/2 (50)

16 HOW SUPPLIED/STORAGE AND HANDLING

Linezolid injection is available in a single-dose, ready-to-use flexible plastic container in a foil laminate overwrap. The container is available in the following package size:

Unit of sale | Concentration
NDC 0409-4883-01; Case of 10 single-dose VisIVTM flexible plastic containers | 600 mg/300 mL; (2 mg/mL)
NDC 0409-4883-10; Case of 10 single-dose freeflex® flexible plastic containers | 600 mg/300 mL; (2 mg/mL)

STORAGE AND HANDLING

Store at 20 to 25°C (68 to 77°F), excursions permitted to 15 to 30°C (59 to 86°F) [see USP Controlled Room Temperature]. Protect from light. It is recommended that the containers be kept in the overwrap until ready to use. Protect containers from freezing.

17 PATIENT COUNSELING INFORMATION

Important Administration Instructions

Advise patients that Linezolid injection may be taken with or without food.

Peripheral and Optic Neuropathy

Advise patients to inform their physician if they experience changes in vision while taking Linezolid injection [see Warnings and Precautions (5.2)].

Serotonin Syndrome

Advise patients to inform their physician if taking serotonergic agents, including serotonin re-uptake inhibitors or other antidepressants and opioids [see Warnings and Precautions (5.3)].

Potential Interactions Producing Elevation of Blood Pressure

- Advise patients to inform their physician if they have a history of hypertension.
- Advise patients to avoid large quantities of foods or beverages with high tyramine content while taking Linezolid injection. Foods high in tyramine content include those that may have undergone protein changes by aging, fermentation, pickling, or smoking to improve flavor, such as aged cheeses, fermented or air-dried meats, sauerkraut, soy sauce, tap beers, and red wines. The tyramine content of any protein-rich food may be increased if stored for long periods or improperly refrigerated.
- Advise patients to inform their physician if taking medications containing pseudoephedrine HCl, such as cold remedies and decongestants [see Warnings and Precautions (5.6)].

Lactic Acidosis

Advise patients to inform their physician if they experience repeated episodes of nausea or vomiting while receiving Linezolid injection [see Warnings and Precautions (5.7)].

Convulsions

Advise patients to inform their physician if they have a history of seizures or convulsions [see Warnings and Precautions (5.8)].

Rhabdomyolysis

Advise patients to inform their physician if they experience signs and symptoms of rhabdomyolysis including muscle pain, tenderness or weakness and dark urine [see Warnings and Precautions (5.9)].

Hypoglycemia

Advise patients to inform their physician if they have diabetes mellitus. Hypoglycemic reactions, such as diaphoresis and tremulousness, along with low blood glucose measurements may occur when treated with linezolid. If such reactions occur, patients should contact a physician or other health professional for proper treatment [see Warnings and Precautions (5.10)].

Hyponatremia and/or SIADH

Advise patients at risk for hyponatremia to inform their physician if they experience signs and symptoms of hyponatremia and/or SIADH, including confusion, somnolence, generalized weakness, and respiratory distress [see Warnings and Precautions (5.11)].

Antibacterial Resistance

Patients should be counseled that antibacterial drugs including Linezolid injection should only be used to treat bacterial infections. They do not treat viral infections (e.g., the common cold). When linezolid injection is prescribed to treat a bacterial infection, patients should be told that although it is common to feel better early in the course of therapy, the medication should be taken exactly as directed. Skipping doses or not completing the full course of therapy may (1) decrease the effectiveness of the immediate treatment and (2) increase the likelihood that bacteria will develop resistance and will not be treatable by linezolid or other antibacterial drugs in the future.

Diarrhea

Diarrhea is a common problem caused by antibacterial drugs, which usually ends when the antibacterial drug is discontinued. Sometimes after starting treatment with antibacterial drugs, patients can develop watery and bloody stools (with or without stomach cramps and fever) even as late as two or more months after having taken the last dose of the antibacterial drug. If this occurs, patients should contact their physician as soon as possible [see Warnings and Precautions (5.5)].

Infertility

Advise male patients that linezolid may reversibly impair fertility [see Use in Specific Populations (8.3)].

Distributed by Hospira, Inc., Lake Forest, IL 60045 USA

LAB-1031-14.0

PRINCIPAL DISPLAY PANEL - 300 mL Bag Label - VisIV™ Container

300 mL
NDC 0409-4883-11

Linezolid Injection
in 0.9% Sodium Chloride
600 mg/300 mL
(2 mg/mL)

For Intravenous Infusion

EACH ML CONTAINS LINEZOLID,
2 MG; CITRIC ACID ANHYDROUS, USP,
1.92 MG; SODIUM HYDROXIDE, 0.76 MG;
SODIUM CHLORIDE, USP 9 MG IN WATER
FOR INJECTION. ADJUST pH TO 4.4 -
5.2 WITH SODIUM HYDROXIDE AND/OR
HYDROCHLORIC ACID.

STERILE AND NON-PYROGENIC. SINGLE-
DOSE CONTAINER. DOSAGE AND USE:
SEE INSERT. STORE AT 20 TO 25°C
(68 TO 77°F). EXCURSIONS PERMITTED
TO 15 TO 30°C (59 TO 86°F). [SEE USP
CONTROLLED ROOM TEMPERATURE.]
PROTECT FROM FREEZING. LINEZOLID
IS SENSITIVE TO LIGHT. RETAIN
IN OVERWRAP PRIOR TO USE. USE
ONLY IF SOLUTION IS CLEAR AND
CONTAINER IS UNDAMAGED. MUST
NOT BE USED IN SERIES CONNECTIONS.
VisIV IS A TRADEMARK OF HOSPIRA. DO
NOT REMOVE CAPS UNTIL READY FOR
USE. IF LEAKS ARE FOUND, DISCARD
SOLUTION AS STERILITY MAY BE
IMPAIRED.

VisIV™ Container

Rx ONLY

5
PP

IM-5097

HOSPIRA, INC.,
LAKE FOREST, IL 60045 USA

Hospira

SET

PRINCIPAL DISPLAY PANEL - 300 mL Pouch Label - VisIV™ Container

300 mL
NDC 0409-4883-11

Linezolid Injection
in 0.9% Sodium Chloride

600 mg/300 mL
(2 mg/mL)
For Intravenous Infusion

Single-dose container

F WR-1532

Hospira, Inc., Lake Forest, IL 60045 USA
Hospira

PRINCIPAL DISPLAY PANEL - 300 mL Bag Label - freeflex® containers

300 mL
NDC 0409-4883-03

Linezolid Injection
in 0.9% Sodium Chloride
600 mg/300 mL
(2 mg/mL)
For Intravenous Infusion

Each mL contains Linezolid 2 mg; Citric Acid anhydrous, USP,

1.92 mg; Sodium Hydroxide, 0.76 mg; Sodium Chloride, USP 9 mg in

Water for Injection. Adjust pH to 4.4 - 5.2 with Sodium Hydroxide

and/or Hydrochloric Acid.

Sterile and non-pyrogenic. Single-dose container. Recommended Dosage:

See Prescribing Information. Store at 20 to 25°C (68 to 77°F). Excursions

permitted to 15 to 30°C (59 to 86°F). [See USP Controlled Room

Temperature.] Protect from freezing. Linezolid is sensitive to light.

Use only if solution is clear and container is undamaged. Must

not be used in series connections. Do not remove caps until

ready for use. If leaks are found, discard solution as sterility

may be impaired.

Rx ONLY

Hospira

Distributed by Hospira, Inc.
lake Forest, IL 60045 USA

PRINCIPAL DISPLAY PANEL - 300 mL Pouch Label - freeflex® containers

300 mL
NDC 0409-4883-03

Linezolid Injection
in 0.9% Sodium Chloride
600 mg/300 mL (2 mg/mL)

For Intravenous Infusion. Single-dose container

TO OPEN — TEAR AT NOTCH

Each mL contains Linezolid, 2 mg; Citric Acid anhydrous, USP, 1.92 mg;

Sodium Hydroxide, 0.76 mg; Sodium Chloride, USP 9 mg in Water for
Injection. pH adjusted to 4.4 - 5.2 with Sodium Hydroxide and/or
Hydrochloric Acid.

Discard unused portion. Recommended Dosage: See Prescribing
Information.

The overwrap is a moisture barrier. Do not remove unit from overwrap
until ready for use. Visually inspect overwrap for tears or holes. Discard
unit if overwrap is damaged or if solution is discolored in any way. Use
unit promptly when overwrap is opened.

Store at 20 to 25ºC (68 to 77ºF). Excursions permitted to 15 to 30ºC

(59 to 86ºF). [See USP Controlled Room Temperature.] Do not freeze.

Rx only

Linezolid is sensitive to light. After removing the overwrap,
check bag for minute leaks by squeezing container firmly.

If leaks are found, discard solution as sterility may be impaired.
MADE IN SINGAPORE

Distributed by Hospira Inc., Lake Forest, IL 60045 USA

Hospira